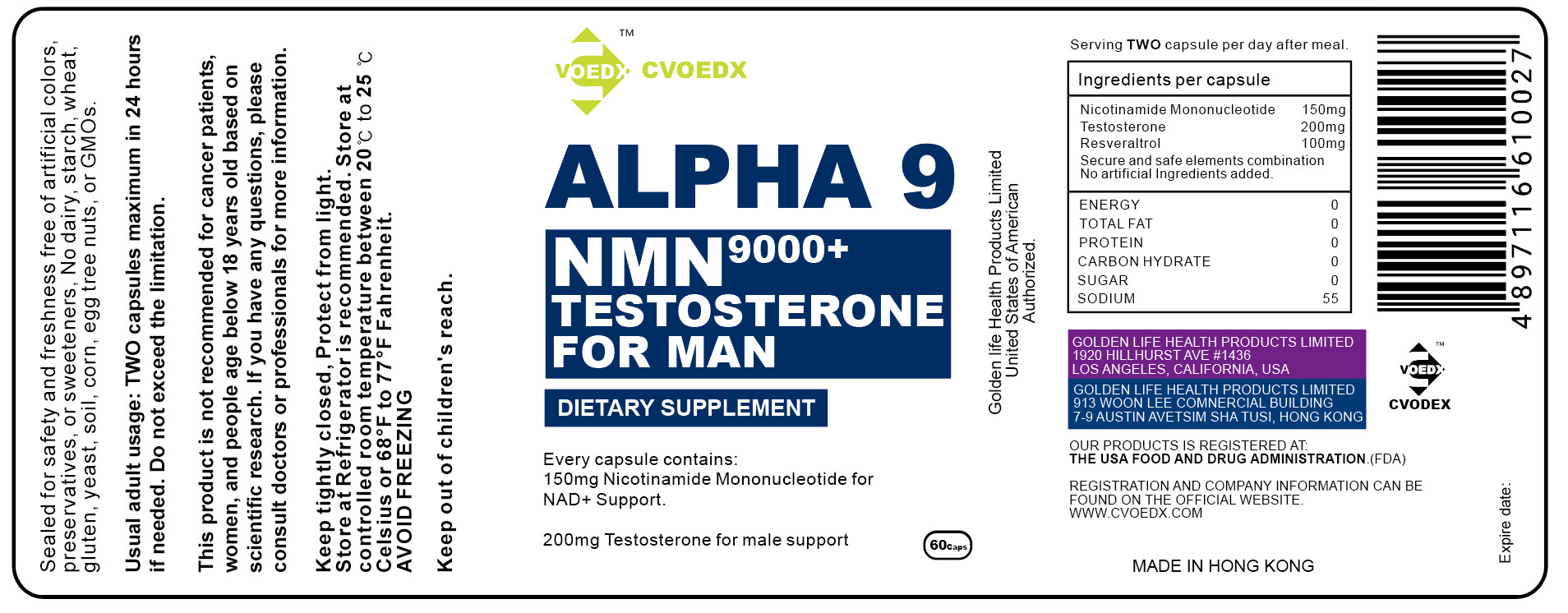 DRUG LABEL: Alpha9
NDC: 11777-003 | Form: POWDER
Manufacturer: Golden Life Health Products Limited
Category: otc | Type: HUMAN OTC DRUG LABEL
Date: 20201225

ACTIVE INGREDIENTS: NICOTINAMIDE RIBOTIDE 33 mg/100 mg; RESVERATROL 22 mg/100 mg; MATRINE 22 mg/100 mg
INACTIVE INGREDIENTS: TESTOSTERONE UNDECANOATE

DOSAGE AND ADMINISTRATION

serving Two capsule per day after meal.

Usual adult usage: Two capsules maximum in 24 hours if needed. Do not exceed the limitation.

information

Keep tightly closed, Protect from light.
Store at Refrigerator is recommended. Store at controlled room temperature between 20℃ to 25 ℃ celsius or 68°F to 77°F Fahrenheit

INDICATIONS AND USAGE

This product is not recommended for cancer patients,women, and people age below 18 years oldbased on scientific research. lf you have any questions,please consult doctors or professionals for more information.

INACTIVE INGREDIENT

Testosterone

ACTIVE INGREDIENT

matrine 22%

Nicotinamide mononucleotide 33%
Resveraltrol 22%

Keep out of children's reach.

PURPOSE

Every capsule contains:

150mg Nicotinamide Mononucleotide for NAD+ Support.
200mg Testosterone for male support

WARNINGS

Sealed for safety and freshness free of artificial colors,preservatives , or sweeteners, No dairy, starch, wheat,gluten, yeast, soil, corn, egg tree nuts, or GMOs.